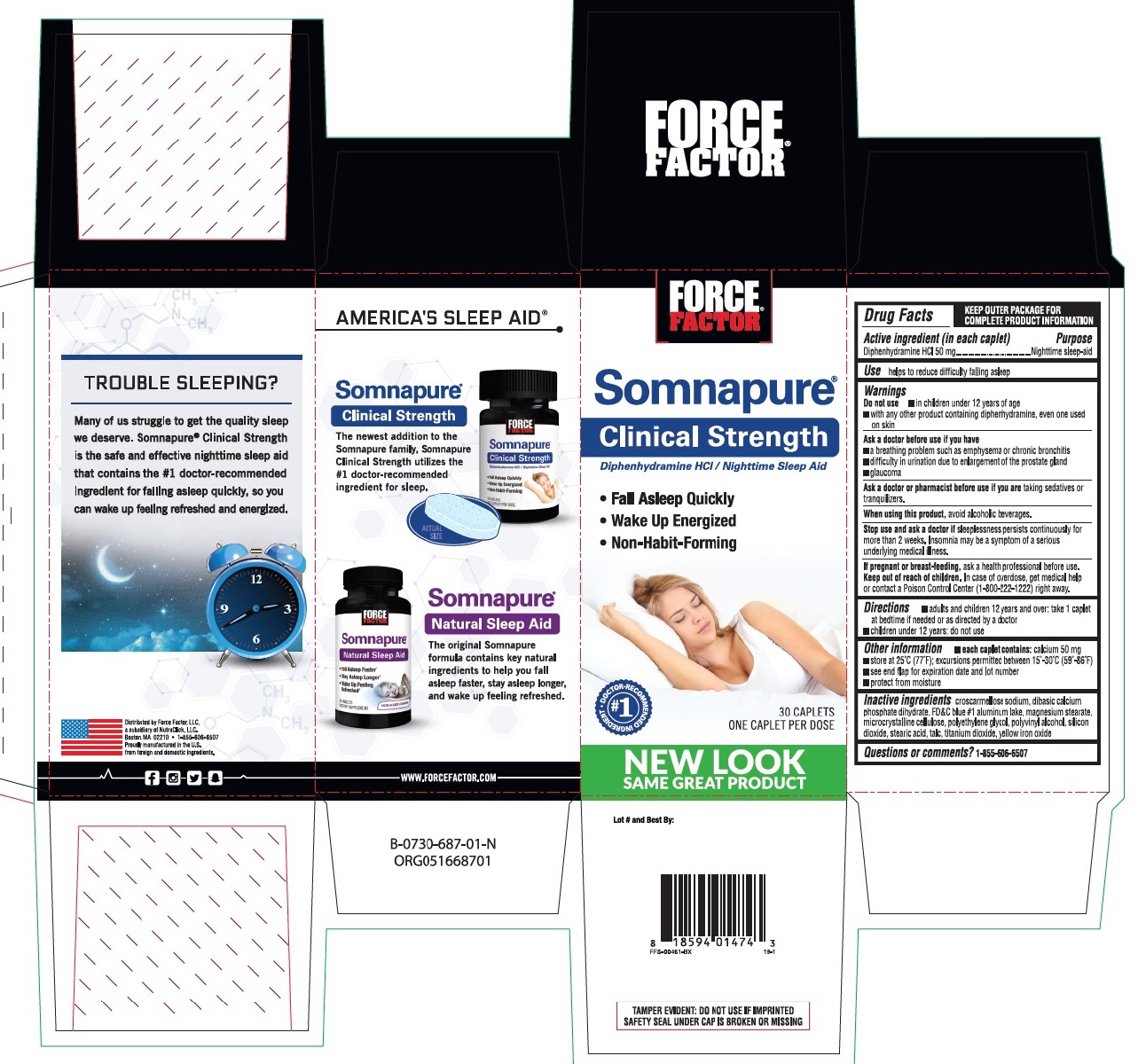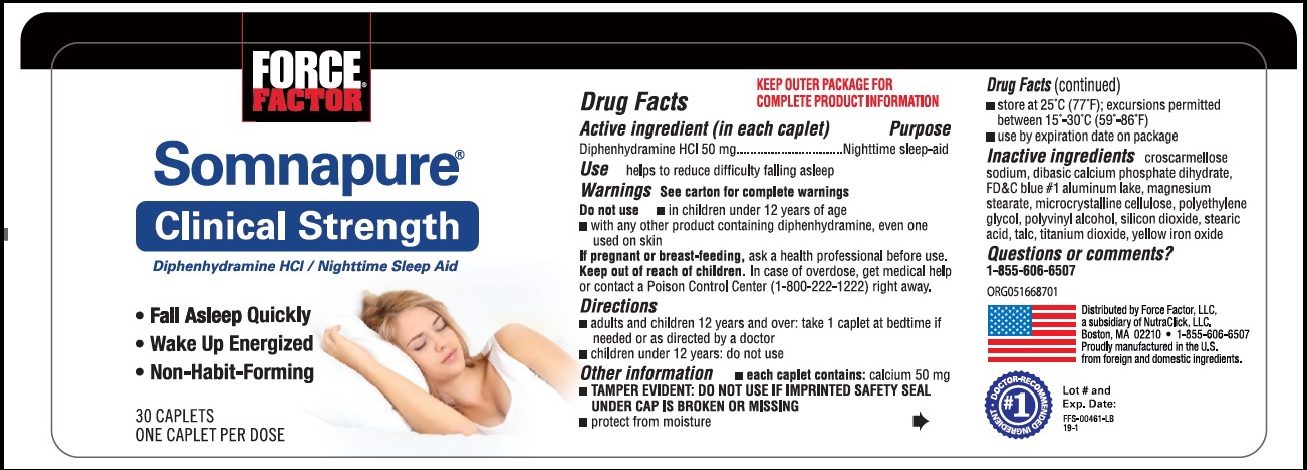 DRUG LABEL: Somnapure
NDC: 69721-005 | Form: TABLET, COATED
Manufacturer: Force Factor Brands LLC
Category: otc | Type: HUMAN OTC DRUG LABEL
Date: 20241206

ACTIVE INGREDIENTS: DIPHENHYDRAMINE HYDROCHLORIDE 50 mg/1 1
INACTIVE INGREDIENTS: CROSCARMELLOSE SODIUM; DIBASIC CALCIUM PHOSPHATE DIHYDRATE; FD&C BLUE NO. 1 ALUMINUM LAKE; MAGNESIUM STEARATE; MICROCRYSTALLINE CELLULOSE; POLYETHYLENE GLYCOL, UNSPECIFIED; POLYVINYL ALCOHOL, UNSPECIFIED; SILICON DIOXIDE; STEARIC ACID; TALC; TITANIUM DIOXIDE; FERRIC OXIDE YELLOW

Somnapure Clinical Strength

Drug Facts

Active ingredient (in each caplet)

Diphenhydramine HCl 50 mg

Purpose

Nighttime sleep aid

Use

helps to reduce difficulty in falling asleep

Warnings

Do not use

- in children under 12 years of age
- with any other product containing diphenhydramine, even one used on skin

Ask a doctor before use if you have

- a breathing problem such as emphysema or chronic bronchitis
- glaucoma
- difficulty in urination due to enlargement of the prostate gland

Ask a doctor or pharmacist before use if you are taking sedatives or tranquilizers.

When using this product, avoid alcoholic beverages.

Stop use and ask a doctor if sleeplessness persists continuously for more than 2 weeks. Insomnia may be a symptom of a serious underlying medical illness.

PREGNANCY OR BREAST FEEDING

If pregnant or breastfeeding, ask a health professional before use.

Keep out of reach of children. In case of overdose, get medical help or contact a Poison Control Center (1-800-222-1222) right away.

Directions

- adults and children 12 years and over: take 1 caplet at bedtime if needed or as directed by a doctor
- Children under 12 years: do not use.

Other information

- each caplet contains: calcium 50 mg
- store at 25°C (77°F); excursions permitted between 15°-30°C (59°-86°F)
- see end flap for expiration date and lot number.
- protect from moisture

INACTIVE INGREDIENT

Inactive ingredients croscarmellose sodium, dibasic calcium phosphate dihydrate, FD&C blue #1 aluminum lake, magnesium stearate, microcrystalline cellulose, polyethylene glycol, polyvinyl alcohol, silcon dioxide, stearic acid, talc, titanium dioxide, yellow iron oxide

Questions of comments? Call 1-855-606-6507

Principal display panel

Force Factor Somnapure

Clinical Strength

Nighttime Sleep Aid / Diphenhydramine HCl

#1 Doctor-Recommended Ingredient

Fall Asleep Quickly
Wake Up Energized
Non-Habit-Forming

30 Caplets

One Caplet per Dose